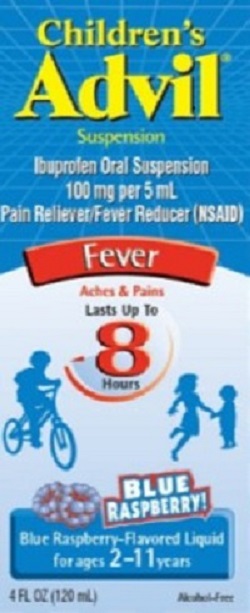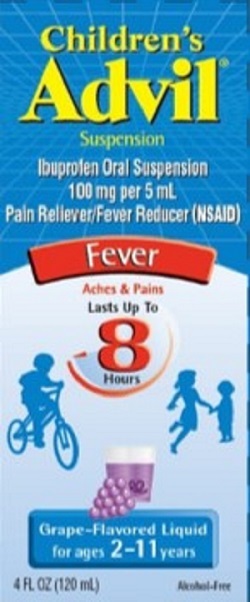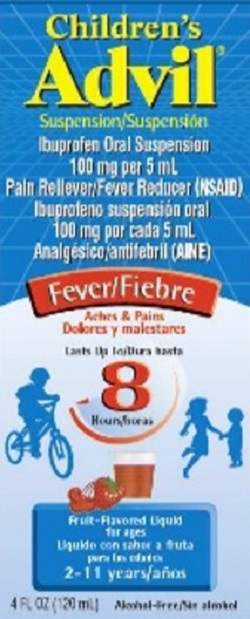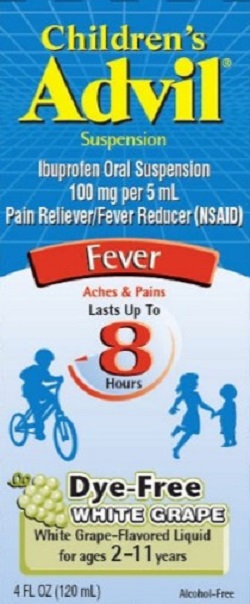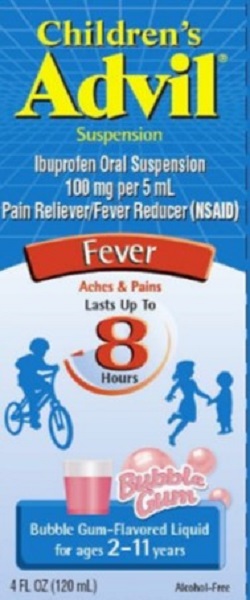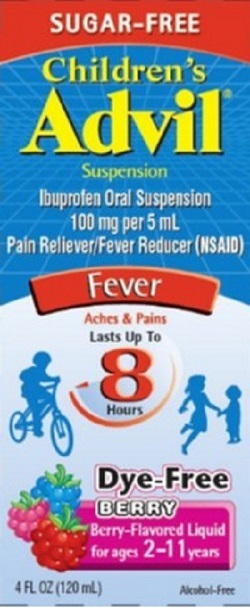 DRUG LABEL: CHILDRENS ADVIL
NDC: 0573-0174 | Form: SUSPENSION
Manufacturer: Haleon US Holdings LLC
Category: otc | Type: HUMAN OTC DRUG LABEL
Date: 20240208

ACTIVE INGREDIENTS: IBUPROFEN 100 mg/5 mL
INACTIVE INGREDIENTS: CARBOXYMETHYLCELLULOSE SODIUM, UNSPECIFIED; CITRIC ACID MONOHYDRATE; EDETATE DISODIUM; FD&C BLUE NO. 1; GLYCERIN; MICROCRYSTALLINE CELLULOSE; POLYSORBATE 80; PROPYLENE GLYCOL; WATER; SODIUM BENZOATE; SODIUM CITRATE, UNSPECIFIED FORM; SORBITOL; SUCROSE; XANTHAN GUM

Drug Facts

ACTIVE INGREDIENT (IN EACH 5 ML)

Ibuprofen 100 mg (NSAID)*

*nonsteroidal anti-inflammatory drug

PURPOSE

Fever reducer/Pain reliever

USES

temporarily:

- reduces fever
- relieves minor aches and pains due to the common cold, flu, sore throat, headaches and toothaches

WARNINGS

Allergy alert:

Ibuprofen may cause a severe allergic reaction, especially in people allergic to aspirin. Symptoms may include:

- hives
- facial swelling
- asthma (wheezing)
- shock
- skin reddening
- rash
- blisters

If an allergic reaction occurs, stop use and seek medical help right away.

Stomach bleeding warning:

This product contains an NSAID, which may cause severe stomach bleeding. The chance is higher if the child

- has had stomach ulcers or bleeding problems
- takes a blood thinning (anticoagulant) or steroid drug
- takes other drugs containing prescription or nonprescription NSAIDs [aspirin, ibuprofen, naproxen, or others]
- takes more or for a longer time than directed

Heart attack and stroke warning

NSAIDs, except aspirin, increase the risk of heart attack, heart failure, and stroke. These can be fatal. The risk is higher if you use more than directed or for longer than directed.

Sore throat warning:

Severe or persistent sore throat or sore throat accompanied by high fever, headache, nausea, and vomiting may be serious. Consult doctor promptly. Do not use more than 2 days or administer to children under 3 years of age unless directed by doctor.

Do not use

- if the child has ever had an allergic reaction to any other pain reliever/fever reducer
- right before or after heart surgery

Ask a doctor before use if

- stomach bleeding warning applies to the child
- child has problems or serious side effects from taking pain relievers or fever reducers
- child has a history of stomach problems, such as heartburn
- child has high blood pressure, heart disease, liver cirrhosis, kidney disease, or asthma, or had a stroke
- child has not been drinking fluids
- child has lost a lot of fluid due to vomiting or diarrhea
- child is taking a diuretic

Ask a doctor or pharmacist before use if the child is

- under a doctor's care for any serious condition
- taking any other drug

When using this product

- take with food or milk if stomach upset occurs

Stop use and ask a doctor if

- child experiences any of the following signs of stomach bleeding:
  - feels faint
  - vomits blood
  - has bloody or black stools
  - has stomach pain that does not get better
- child has symptoms of heart problems or stroke:
  - chest pain
  - trouble breathing
  - weakness in one part or side of body
  - slurred speech
  - leg swelling
- the child does not get any relief within first day (24 hours) of treatment
- fever or pain gets worse or lasts more than 3 days
- redness or swelling is present in the painful area
- any new symptoms appear

Keep out of reach of children.

In case of overdose, get medical help or contact a Poison Control Center right away.

DIRECTIONS

- this product does not contain directions or complete warnings for adult use
- do not give more than directed
- shake well before using
- mL = milliliter
- find right dose on chart below. If possible, use weight to dose; otherwise use age.
- repeat dose every 6-8 hours, if needed
- do not use more than 4 times a day
- measure only with the dosing cup provided. Dosing cup to be used with Children's Advil Suspension only. Do not use with other products. Dose lines account for product remaining in cup due to thickness of suspension.

Dosing Chart

Weight (lb) | Age (yr) | Dose (mL)
under 24 lb | under 2 yr | ask a doctor
24-35 lb | 2-3 yr | 5 mL
36-47 lb | 4-5 yr | 7.5 mL
48-59 lb | 6-8 yr | 10 mL
60-71 lb | 9-10 yr | 12.5 mL
72-95 lb | 11 yr | 15 mL

OTHER INFORMATION

Children's Advil Suspension Fruit Flavor; Children's Advil Suspension Grape Flavor; Children's Advil Suspension White Grape Flavor; Children's Advil Bubblegum

- each 5 mL contains: sodium 3 mg
- one dose lasts 6-8 hours
- store at 20-25°C (68-77°F)
- see bottom of box for lot number and expiration date

Children's Advil Suspension Blue Raspberry Flavor; Children's Advil Suspension Sugar-Free Dye-Free Berry Flavor

- each 5 mL contains: sodium 10 mg
- one dose lasts 6-8 hours
- store at 20-25°C (68-77°F)
- see bottom of box for lot number and expiration date

INACTIVE INGREDIENTS

Children's Advil Suspension Fruit Flavor

artificial flavor, carboxymethylcellulose sodium, citric acid monohydrate, edetate disodium, FD&C red no. 40, glycerin, microcrystalline cellulose, polysorbate 80, purified water, sodium benzoate, sorbitol solution, sucrose, xanthan gum

Children's Advil Suspension Grape Flavor

acetic acid, artificial flavor, butylated hydroxytoluene, carboxymethylcellulose sodium, citric acid monohydrate, edetate disodium, FD&C blue no.1, FD&C red no. 40, glycerin, microcrystalline cellulose, polysorbate 80, propylene glycol, purified water, sodium benzoate, sorbitol solution, sucrose, xanthan gum

Children's Advil Suspension Blue Raspberry Flavor

artificial and natural flavors, carboxymethylcellulose sodium, citric acid monohydrate, edetate disodium, FD&C blue no. 1, glycerin, microcrystalline cellulose, polysorbate 80, propylene glycol, purified water, sodium benzoate, sodium citrate, sorbitol solution, sucrose, xanthan gum

Children's Advil Suspension White Grape Flavor

acetic acid, artificial flavor, butylated hydroxytoluene, carboxymethylcellulose sodium, citric acid monohydrate, edetate disodium, glycerin, microcrystalline cellulose, polysorbate 80, propylene glycol, purified water, sodium benzoate, sorbitol solution, sucrose, xanthan gum

Children's Advil Suspension Bubblegum Flavor

carboxymethylcellulose sodium, citric acid monohydrate, edetate disodium, FD&C red no. 40, glycerin, microcrystalline cellulose, natural and artificial flavor, polysorbate 80, propylene glycol, purified water, sodium benzoate, sorbitol solution, sucrose, xanthan gum

Children's Advil Suspension Sugar-Free Dye-Free Berry

artificial flavor, +orbate 80, propylene glycol, purified water, sodium benzoate, sodium citrate, sorbitol solution, sucralose, xanthan gum

QUESTIONS OR COMMENTS?

call toll-free 1-800-88-ADVIL or ask your pharmacist, doctor or health care professional

PRINCIPAL DISPLAY PANEL

NDC 0573-0174-30

Children's
Advil®
Suspension

Ibuprofen Oral Suspension
100 mg per 5 mL
Pain Reliever/Fever Reducer (NSAID)

Fever

Aches & Pains
Lasts Up To
8
Hours

BLUE
RASPBERRY!

Blue Raspberry-Flavored Liquid
for ages 2-11 years

4 FL OZ (120 mL)
Alcohol-Free

PRINCIPAL DISPLAY PANEL

NDC 0573-0171-30

Children's
Advil®
Suspension

Ibuprofen Oral Suspension
100 mg per 5 mL
Pain Reliever/Fever Reducer (NSAID)

Fever

Aches & Pains
Lasts Up To
8
Hours

Grape-Flavored Liquid
for ages 2-11 years

4 FL OZ (120 mL)
Alcohol-Free

PRINCIPAL DISPLAY PANEL

NDC 0573-0170-30

Children's
Advil®
Suspension

Ibuprofen Oral Suspension
100 mg per 5 mL
Pain Reliever/Fever Reducer (NSAID)

Fever

Aches & Pains

Lasts Up To
8
Hours

Fruit-Flavored Liquid
for ages
2-11 years

4 FL OZ (120 mL)
Alcohol-Free

PRINCIPAL DISPLAY PANEL

NDC0573-0290-30

Children's
Advil®
Suspension

Ibuprofen Oral Suspension
100 mg per 5 mL
Pain Reliever/Fever Reducer (NSAID)

Fever

Aches & Pains
Lasts Up To
8
Hours

Dye-Free
WHITE GRAPE

White Grape-Flavored Liquid
for ages 2-11 years

4 FL OZ (120 mL)
Alcohol-Free

PRINCIPAL DISPLAY PANEL

NDC 0573-0207-30

Children's
Advil®
Suspension

Ibuprofen Oral Suspension
100 mg per 5 mL
Pain Reliever/Fever Reducer (NSAID)

Fever

Aches & Pains
Lasts Up To
8
Hours

Bubble
Gum

Bubble Gum-Flavored Liquid
for ages 2-11 years

4 FL OZ (120 mL)
Alcohol-Free

PRINCIPAL DISPLAY PANEL

NDC 0573-0232-30

SUGAR-FREE

Children's
Advil®
Suspension

Ibuprofen Oral Suspension
100 mg per 5 mL
Pain Reliever/Fever Reducer (NSAID)

Fever

Aches & Pains
Lasts Up To
8
Hours

Dye-Free
BERRY

Berry-Flavored Liquid
for ages 2-11 years

4 FL OZ (120 mL)
Alcohol-Free